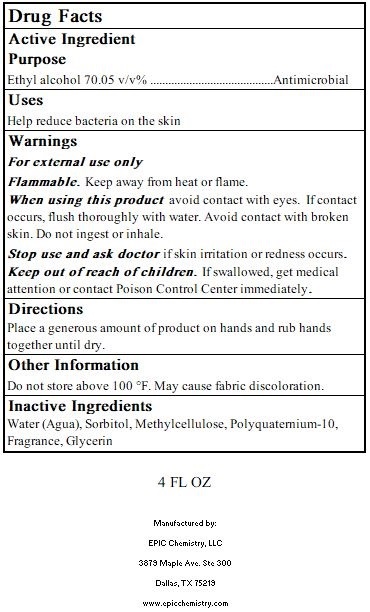 DRUG LABEL: EHS7000-4
NDC: 77022-1114 | Form: GEL
Manufacturer: Epic Chemistry LLC
Category: otc | Type: HUMAN OTC DRUG LABEL
Date: 20201230

ACTIVE INGREDIENTS: ALCOHOL 70.05 1/1 1
INACTIVE INGREDIENTS: METHYLCELLULOSE, UNSPECIFIED 0.6 1/1 1; WATER 33.12 1/1 1; GLYCERIN 0.38 1/1 1; POLYQUATERNIUM-10 (30000 MPA.S AT 2%) 0.6 1/1 1; SORBITOL 1.13 1/1 1

4 OZ

Active Ingredient

Ethyl Alcohol 70.05 v/v% Antimicrobial

Usage

Help reduce bacteria on the skin

Directions

Place a generous amount of product on hands and rub hands together until dry.

Other Information

Do not store above 100° F. May cause fabric discoloration.

Inactive Ingredients

Water (Agua), Sorbitol, Methycellulose, Polyquaternium-10, Fragrance, Glycerin

Dosage

Use a liberal amount in palm of hand.

Notice

Keep out of reach of children.

Indications & Usage

For use when soap and water are not available, or in addition to.

Purpose

To cleanse hands when water and soap are not available.

Warnings

For external use only

Flammable. Keep away from heat or flame.

When using this product avoid contact with eyes. If contact occurs, flush thoroughly with water. Avoid contact with broken skin. Do not ingest or inhale.

Stop use and ask doctor if skin irritation or redness occurs.

Keep out of reach of children. If swallowed, seek medical attention or contact Poison Control Center immediately.

Warnings

For external use only

Flammable. Keep away from heat or flame.

When using this product avoid contact with eyes. If contact occurs, flush thoroughly with water. Avoid contact with broken skin. Do not ingest or inhale.

Stop use and ask doctor if skin irritation or redness occurs.

Keep out of reach of children. If swallowed, seek medical attention or contact Poison Control Center immediately.

Warnings

Use as directed.